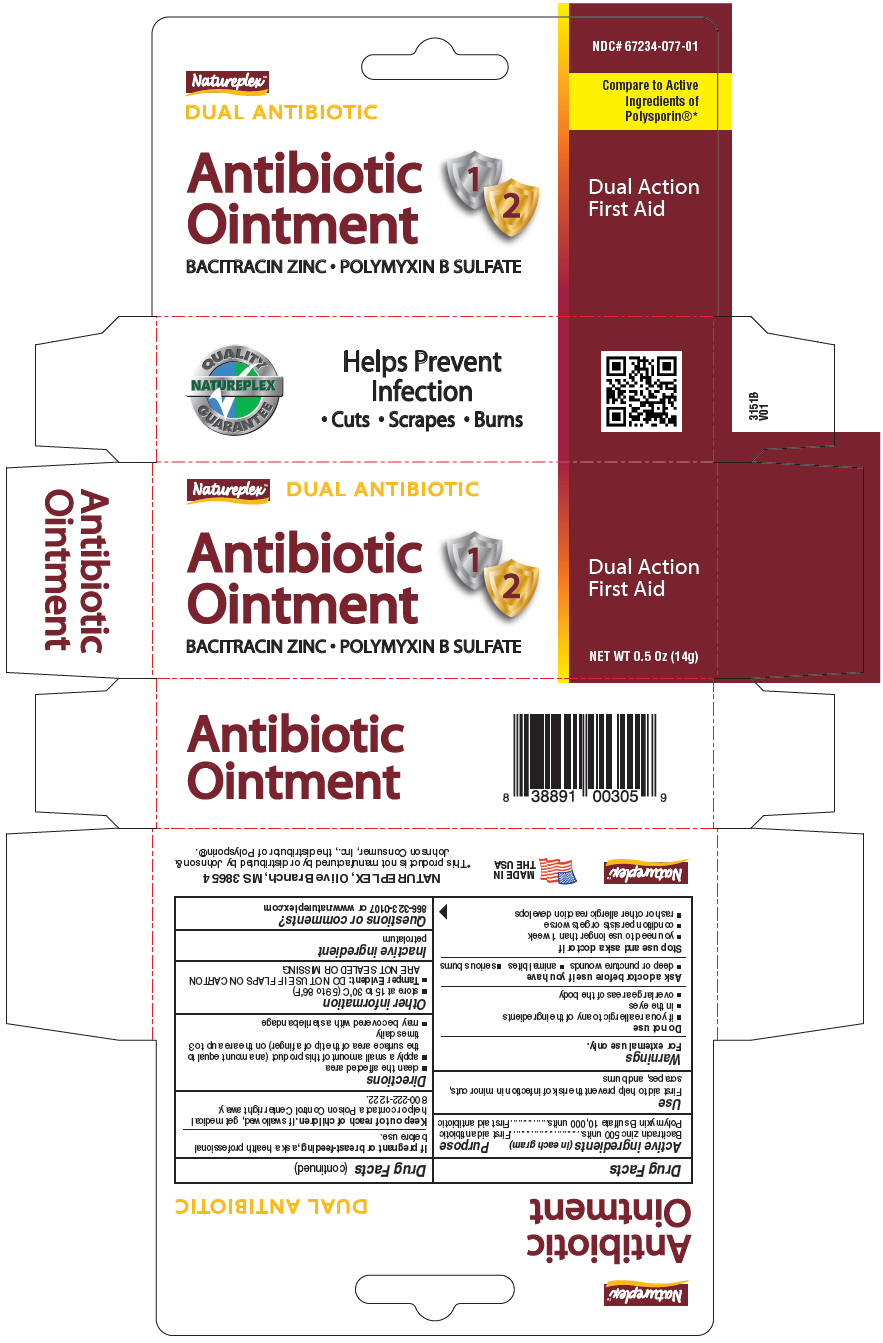 DRUG LABEL: NATUREPLEX ANTIBIOTIC
NDC: 67234-077 | Form: CREAM
Manufacturer: Natureplex LLC
Category: otc | Type: HUMAN OTC DRUG LABEL
Date: 20250115

ACTIVE INGREDIENTS: BACITRACIN ZINC 500 U/14 g; POLYMYXIN B SULFATE 10000 U/14 g
INACTIVE INGREDIENTS: PETROLATUM

NATUREPLEX™ ANTIBIOTIC OINTMENT

Drug Facts

ACTIVE INGREDIENT

Active ingredients (in each gram) | Purpose
Bacitracin zinc 500 units | First aid antibiotic
Polymyxin B sulfate 10,000 units | First aid antibiotic

Use

First aid to help prevent the risk of infection in minor cuts, scrapes, and burns

Warnings

For external use only.

Do not use

- if you are allergic to any of the ingredients
- in the eyes
- over large areas of the body

Ask a doctor before use if you have

- deep or puncture wounds
- animal bites
- serious burns

Stop use and ask a doctor if

- you need to use longer than 1 week
- condition persists or gets worse
- rash or other allergic reaction develops

PREGNANCY OR BREAST FEEDING

If pregnant or breast-feeding, ask a health professional before use.

Keep out of reach of children. If swallowed, get medical help or contact a Poison Control Center right away: 800-222-1222.

Directions

- clean the affected area
- apply a small amount of this product (an amount equal to the surface area of the tip of a finger) on the area up to 3 times daily
- may be covered with a sterile bandage

Other information

- store at 15 to 30°C (59 to 86°F)
- Tamper Evident: DO NOT USE IF FLAPS ON CARTON ARE NOT SEALED OR MISSING

Inactive ingredient

petrolatum

Questions or comments?

866-323-0107 or www.natureplex.com

PRINCIPAL DISPLAY PANEL - 14 g Tube Carton

Natureplex™
DUAL ANTIBIOTIC

Antibiotic
Ointment
1
2

BACITRACIN ZINC • POLYMYXIN B SULFATE

Dual Action
First Aid

NET WT 0.5 Oz (14g)